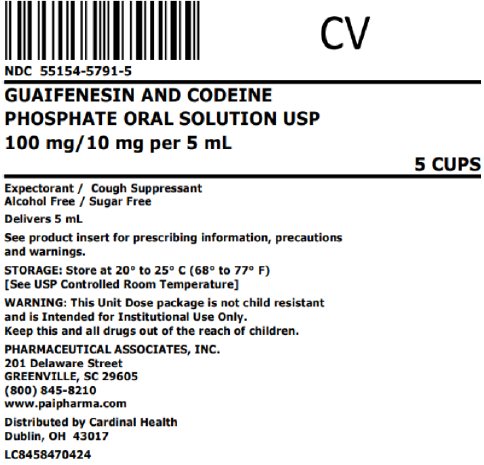 DRUG LABEL: Guaifenesin and Codeine Phosphate
NDC: 55154-5791 | Form: SOLUTION
Manufacturer: Cardinal Health 107, LLC
Category: otc | Type: HUMAN OTC DRUG LABEL
Date: 20251003
DEA Schedule: CV

ACTIVE INGREDIENTS: CODEINE PHOSPHATE 10 mg/5 mL; GUAIFENESIN 100 mg/5 mL
INACTIVE INGREDIENTS: SODIUM CITRATE, UNSPECIFIED FORM; EDETATE DISODIUM; FD&C BLUE NO. 1; FD&C RED NO. 40; FD&C YELLOW NO. 6; GLYCERIN; MENTHOL, UNSPECIFIED FORM; PROPYLENE GLYCOL; WATER; SODIUM BENZOATE; ANHYDROUS CITRIC ACID; SACCHARIN SODIUM; SORBITOL

Guaifenesin and Codeine Phosphate

Drug Facts

ACTIVE INGREDIENT

PURPOSE

Active ingredients in each 5 mL (teaspoonful) | Purposes
Codeine Phosphate, USP 10 mg | Cough Suppressant
Guaifenesin, USP 100 mg | Expectorant

Uses

- temporarily relieves cough due to minor throat and bronchial irritations as may occur with the common cold or inhaled irritants
- helps loosen phlegm (mucus) and thin bronchial secretions to make cough more productive

Warnings

Do not use

- in adults and children who have a chronic pulmonary disease or shortness of breath, or children who are taking other drugs, unless directed by a doctor.

Ask a doctor before use if you have

- a cough with too much phlegm (mucus)
- a persistent or chronic cough as occurs with smoking, asthma, chronic bronchitis, or emphysema

Ask a doctor or pharmacist before use if you aretaking sedatives, tranquilizers and drugs used for depression, especially monoamine oxidase inhibitors (MAOIs). These combinations may cause greater sedation (drowsiness) than is caused by the product used alone.

Stop use and ask a doctor if

- cough lasts for more than 7 days, comes back, or occurs with fever, rash or headache that lasts. These can be signs of a serious condition.
- may cause or aggravate constipation

PREGNANCY OR BREAST FEEDING

If pregnant or breast-feeding,ask a health professional before use.

Keep out of reach of children.In case of accidental overdose, seek professional assistance or contact a Poison Control Center immediately.

- Use of codeine-containing preparation is not recommended for children under 2 years of age.

Directions

- take every 4 hours
- do not exceed 6 doses in 24 hours
- a special measuring device should be used to give an accurate dose of this product to children under 6 years of age
- giving a higher dose than recommended by a doctor can result in serious side effects for a child

adults and children 12 years and over | 10 mL (2 teaspoonfuls)
children 6 to under 12 years of age | 5 mL (1 teaspoonful)
children under 6 years of age | Consult a doctor

Other information

- Sodium Content:5 mg/5 mL
- Tamper evident: Do not use if seal under cap is broken or missing
- Keep container closed and store away from heat
- Store at 20°- 25°C (68°-77°F)

Overbagged with 5 x 5 mL unit-dose cups in each bag, NDC 55154-5791-5

WARNING: This Unit Dose package is not child resistant and is Intended for Institutional Use Only. Keep this and all drugs out of the reach of children.

Inactive ingredients

Citric acid, edetate disodium, FD&C Blue No. 1, FD&C Red No. 40, FD&C Yellow No. 6, flavor, glycerin, menthol, propylene glycol, purified water, sodium benzoate, sodium citrate, sodium saccharin and sorbitol.

Questions or comments?

Call 1-800-845-8210 or visit paipharma.com

Serious side effects associated with use of this product may be reported to this number.

.

Distributed By:

Cardinal Health

Dublin, OH 43017

LC8458470424

Principal Display Panel

CV

NDC 55154-5791-5

GUAIFENESIN AND CODEINE

PHOSPHATE ORAL SOLUTION USP

100 mg/10 mg per 5 mL

5 CUPS